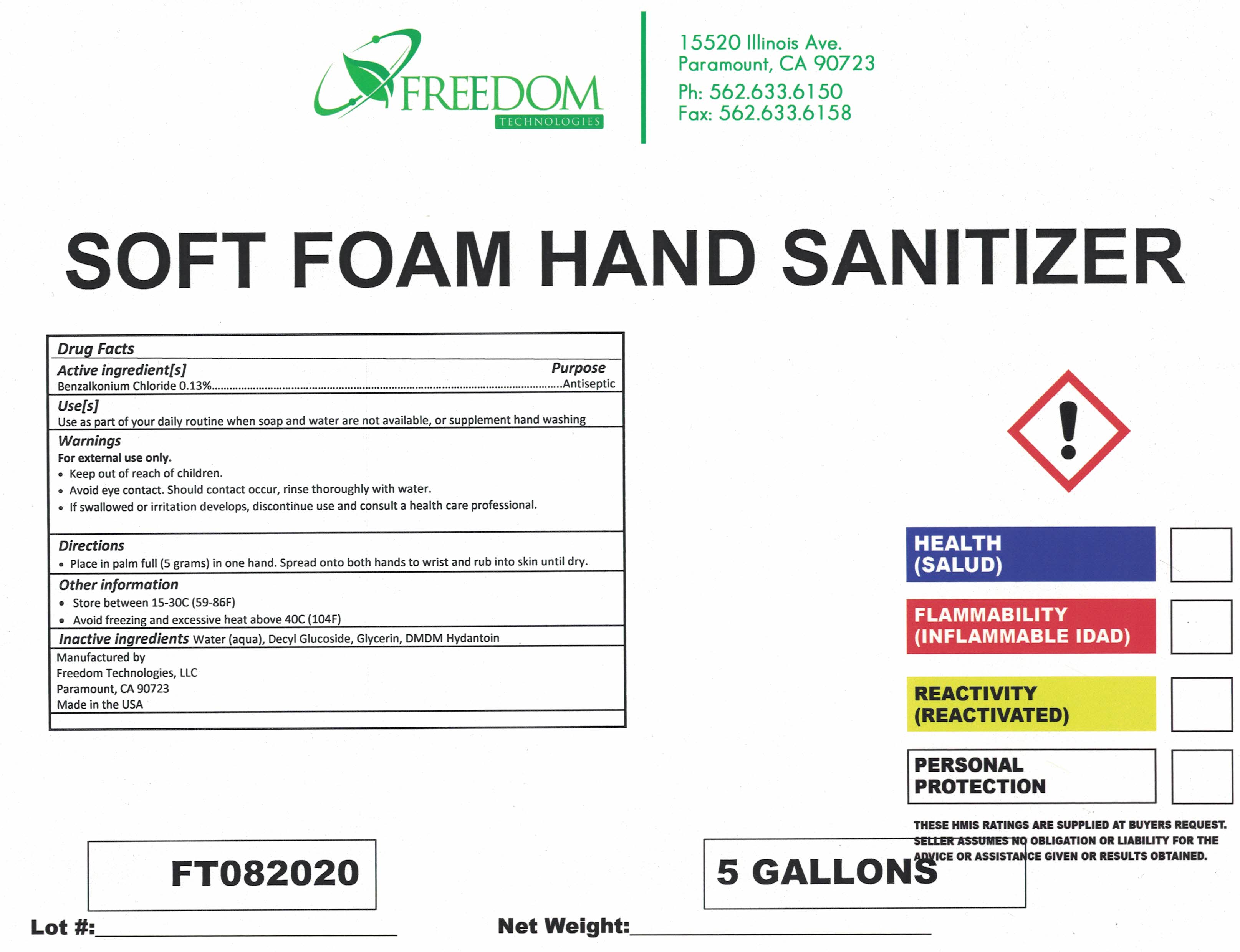 DRUG LABEL: Soft Foam Hand Sanitizer
NDC: 80891-234 | Form: LIQUID
Manufacturer: Freedom Technologies LLC
Category: otc | Type: HUMAN OTC DRUG LABEL
Date: 20220113

ACTIVE INGREDIENTS: BENZALKONIUM CHLORIDE 0.0013 mg/0.0013 mg
INACTIVE INGREDIENTS: DECYL GLUCOSIDE; GLYCERIN; DMDM HYDANTOIN; WATER

Soft Foam Hand Sanitizer

ACTIVE INGREDIENT

Benzalkonium Chloride

PURPOSE

Antibacterial

INDICATIONS AND USAGE

Antibacertial foaming hand cleaner. Use in daycare, nursing homes, restaurants, doctors offices, dental offices, schools and clinics

WARNINGS

For external use only. Avoid contact with eyes. If contact occurs, rinse with water. Discontinue use if irritation or redness develops. If irritation persist for more than 72 hours, consult a physician.

KEEP OUT OF REACH OF CHILDREN. If swallowed, get medical help or contact a Poison control Center right away.

DOSAGE AND ADMINISTRATION

Ready to use without dilution. Dispense 1 pump of product onto plalm of hand and rub thoroughly over all surfaces of hands unitl dry.

INACTIVE INGREDIENT

Water, Decyl Glucoside, Glycerin, DMDM Hydantoin.